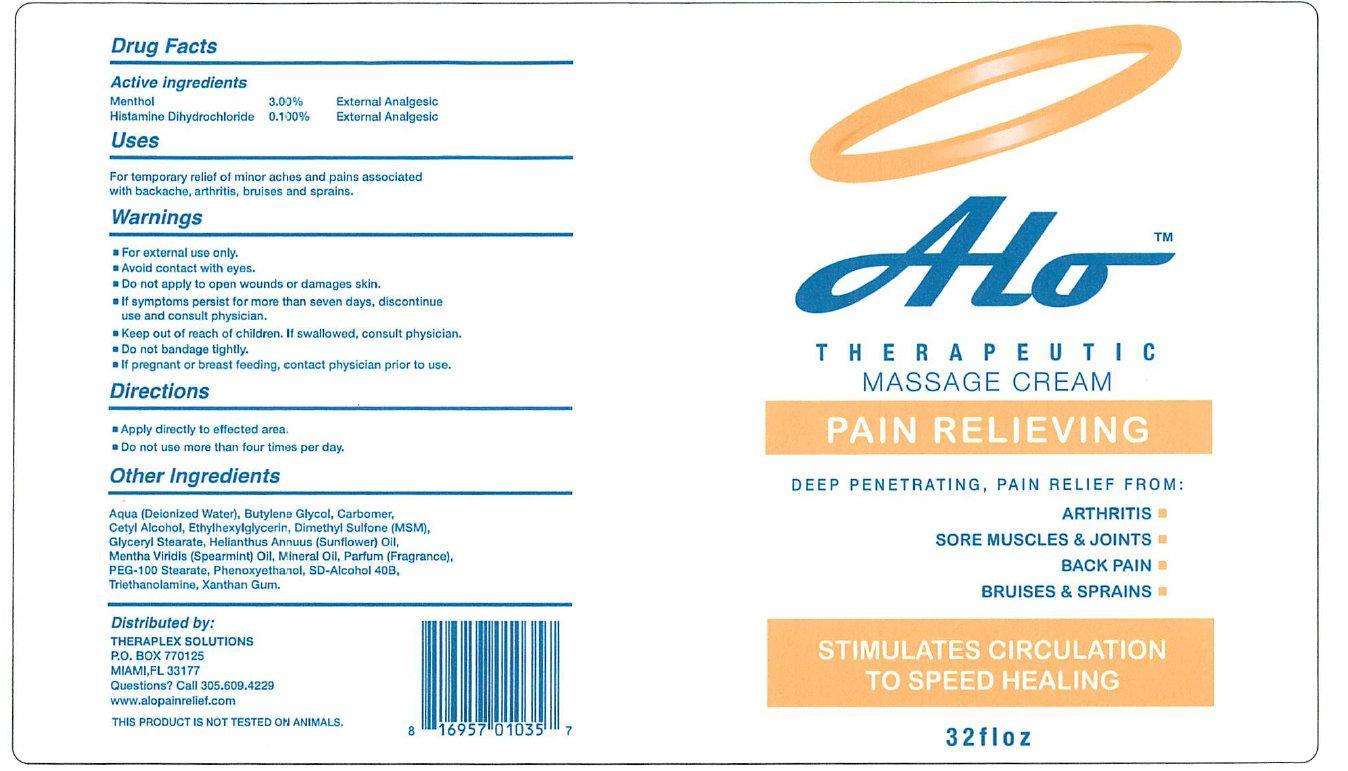 DRUG LABEL: ALO THERAPEUTIC MASSAGE PAIN RELIEVING
NDC: 51457-001 | Form: CREAM
Manufacturer: Theraplex Solutions
Category: otc | Type: HUMAN OTC DRUG LABEL
Date: 20231110

ACTIVE INGREDIENTS: MENTHOL 3 g/100 g; HISTAMINE DIHYDROCHLORIDE 0.1 g/100 g
INACTIVE INGREDIENTS: WATER; BUTYLENE GLYCOL; CETYL ALCOHOL; ETHYLHEXYLGLYCERIN; DIMETHYL SULFONE; GLYCERYL MONOSTEARATE; MINERAL OIL; PEG-100 STEARATE; PHENOXYETHANOL; TROLAMINE; XANTHAN GUM

ALO THERAPEUTIC MASSAGE CREAM PAIN RELIEVING

Active ingredients

Menthol 3.00% Histamine Dihydrochloride 0.100%

Purpose

External Analgesic

Uses

For temporary relief of minor aches and pains associated with backache, arthritis, bruises and sprains.

Warnings

- For external use only.
- Avoid contact with eyes.

• Do not apply

to open wounds or damaged skin.

• If symptoms persist for more than seven days,

discontinue use and consult physician.

• Keep out of reach of children.

If swallowed, consult physician.

• If pregnant or breast feeding,

contact physician prior to use.

Directions

- Apply directly to effected area.
- Do not use more than four times per day.

Other Ingredients

Aqua (Deionized Water), Butylene Glycol, Carbomer, Cetyl Alcohol, Ethylhexylglycerin, Dimethyl Sulfone (MSM), Glyceryl Stearate, Helianthus Annuus (Sunflower) Oil, Mentha Viridis (Spearmint) Oil, Mineral Oil, Parfum (Fragrance), PEG-100 Stearate, Phenoxyethanol, SD-Alcohol 40B, Triethanolamine, Xanthan Gum.

Distributed by:

THERAPLEX SOLUTIONS P.O. BOX 770125 MIAMI, FL 33177 Questions? Call 305.609.4229 www.alopainrelief.com THIS PRODUCT IS NOT TESTED ON ANIMALS.

PACKAGE LABEL

Alo THERAPEUTIC MASSAGE CREAM PAIN RELIEVING

DEEP PENETRATING, PAIN RELIEF FROM: ARTHRITIS

SORE MUSCLES AND JOINTS

BACK PAIN

BRUISES AND SPRAINS

STIMULATES CIRCULATIONS TO SPEED HEALING

32 f l o z